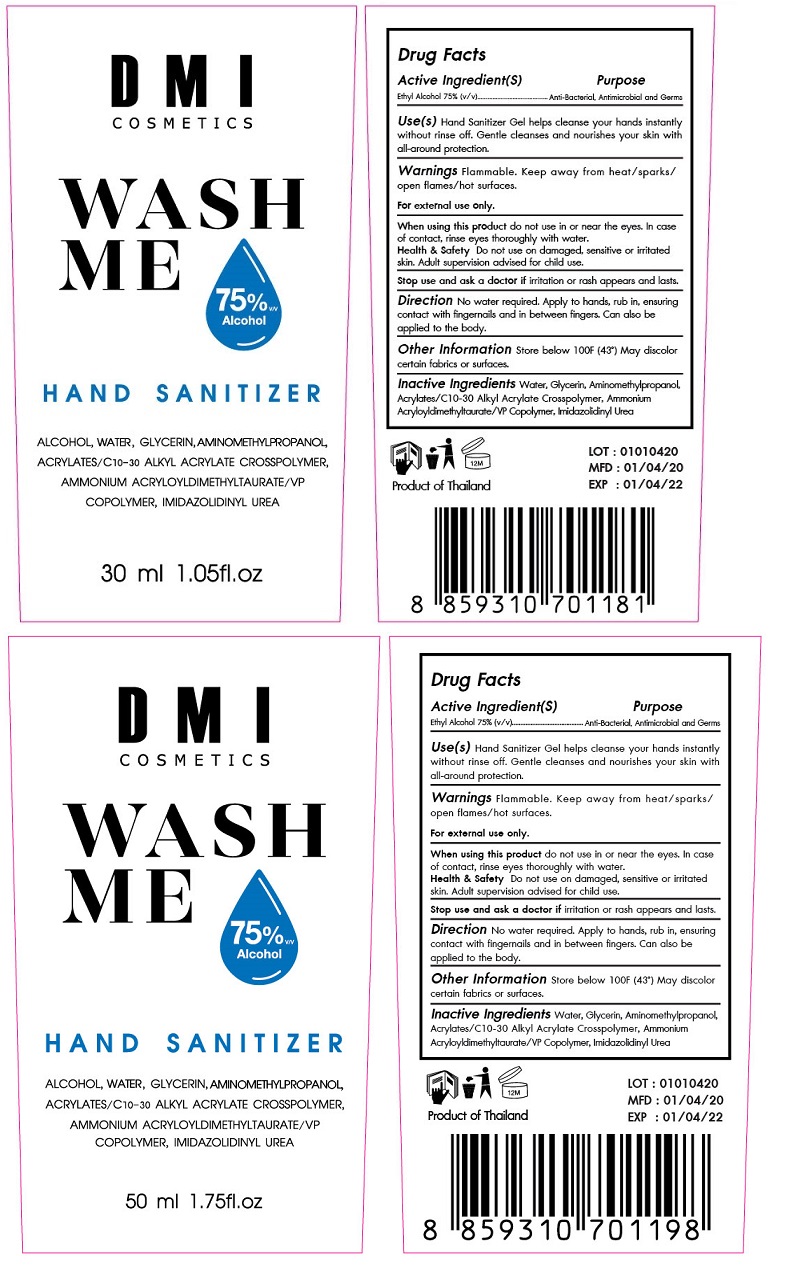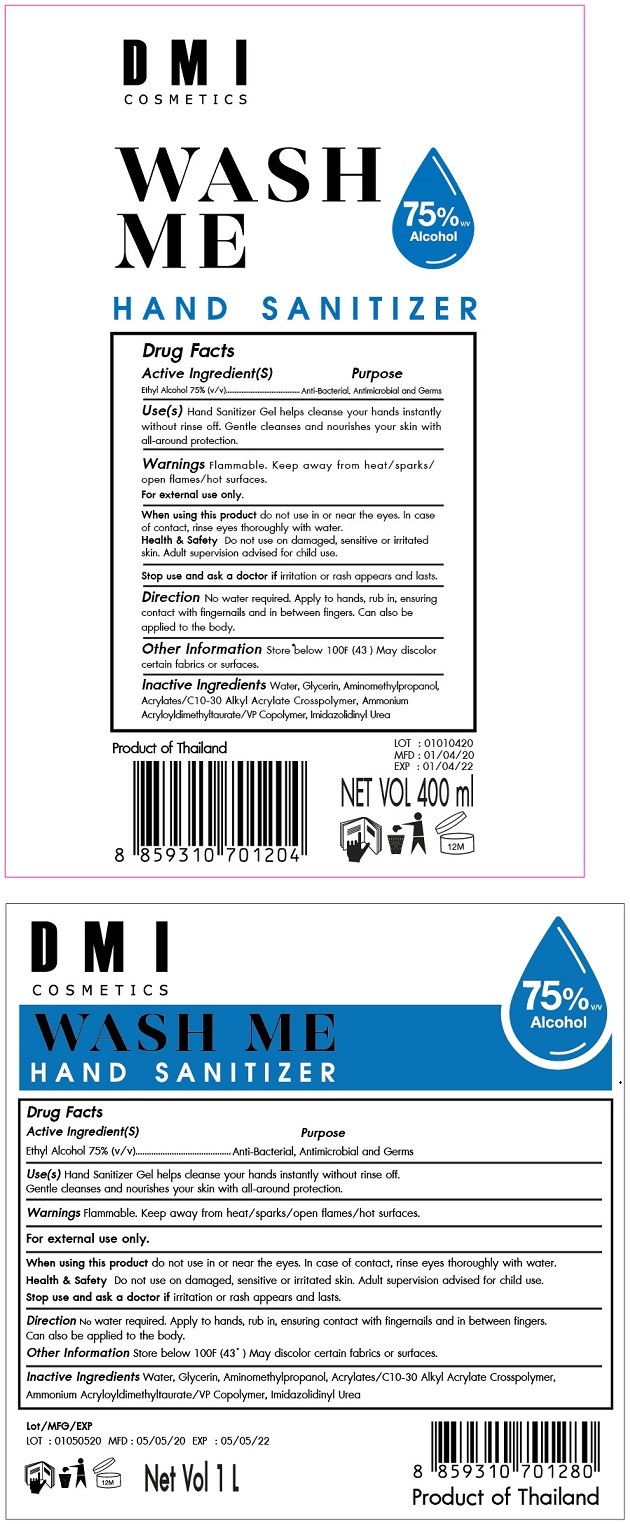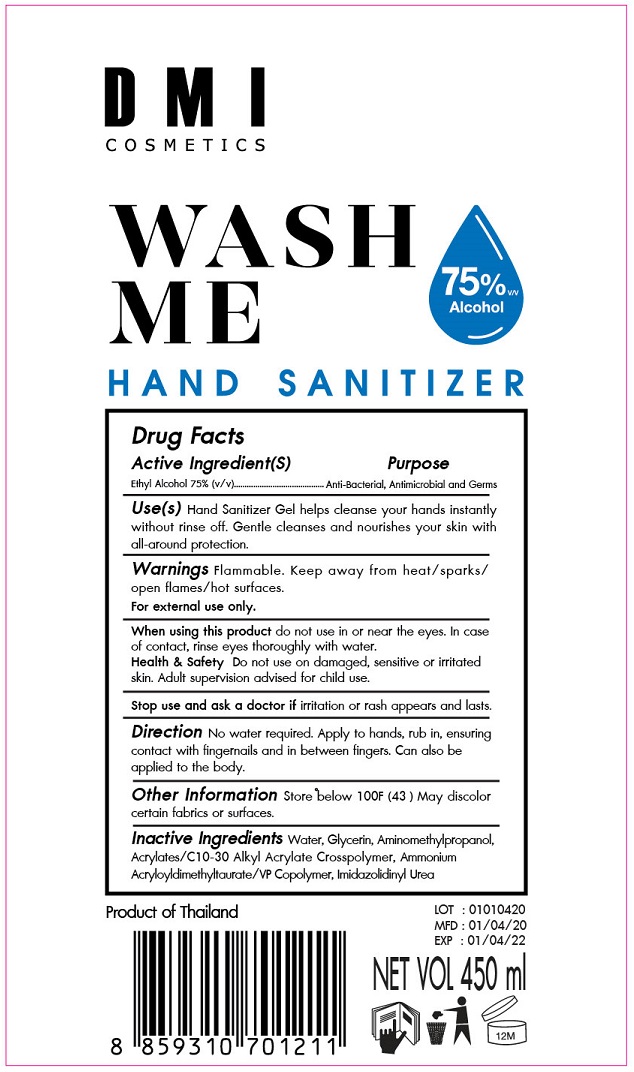 DRUG LABEL: DMI Cosmetics Wash Me Hand Sanitizer
NDC: 77586-001 | Form: GEL
Manufacturer: DERMA INNOVATION COMPANY LIMITED
Category: otc | Type: HUMAN OTC DRUG LABEL
Date: 20200512

ACTIVE INGREDIENTS: ALCOHOL 75 mL/100 mL
INACTIVE INGREDIENTS: WATER; GLYCERIN; AMINOMETHYLPROPANOL; CARBOMER INTERPOLYMER TYPE A (ALLYL SUCROSE CROSSLINKED); AMMONIUM ACRYLOYLDIMETHYLTAURATE/VP COPOLYMER; IMIDUREA

DMI COSMETICS WASH ME HAND SANITIZER

Active Ingredients(s)

Ethyl Alcohol 75% (v/v)

Purpose

Anti-Bacterial, Antimicrobial and Germs

INDICATIONS AND USAGE

Use(s) Hand Sanitizer Gel helps cleanse your hands instantly without rinse off. Gentle cleanses and nourishes your skin with all-round

protection.

WARNINGS

Warnings Flammable. Keep away from heat/ sparks/ open flames / hot surfaces.

For external use only.

When using this product do not use in or near the eyes. In case of contact, rinse eyes thoroughly with water.

Health & Safety Do not use on damaged, sensitive or irritated skin. Adult supervision advised for child use.

Stop use and ask a doctor if irritation or rash appears and lasts.

Keep out of reach of children. If swallowed, get medical help or contact a Poison Control Center right away.

DOSAGE AND ADMINISTRATION

Direction No water required. Apply to hands, rub in, ensuring contact with fingernails and in between fingers. Can also be applied to the body.

Other information Store below 100°F (43°C) May discolor certain fabrics or surfaces.

INACTIVE INGREDIENT

Inactive Ingredients Water, Glycerin, Aminomethylpropanol, Acrylates/C10-30 Alkyl Acrylate Crosspolymer, Ammonium

Acryloyldimethyltaurate/VP Copolymer, Imidazolidinyl Urea

75% Alcohol

Product of Thailand